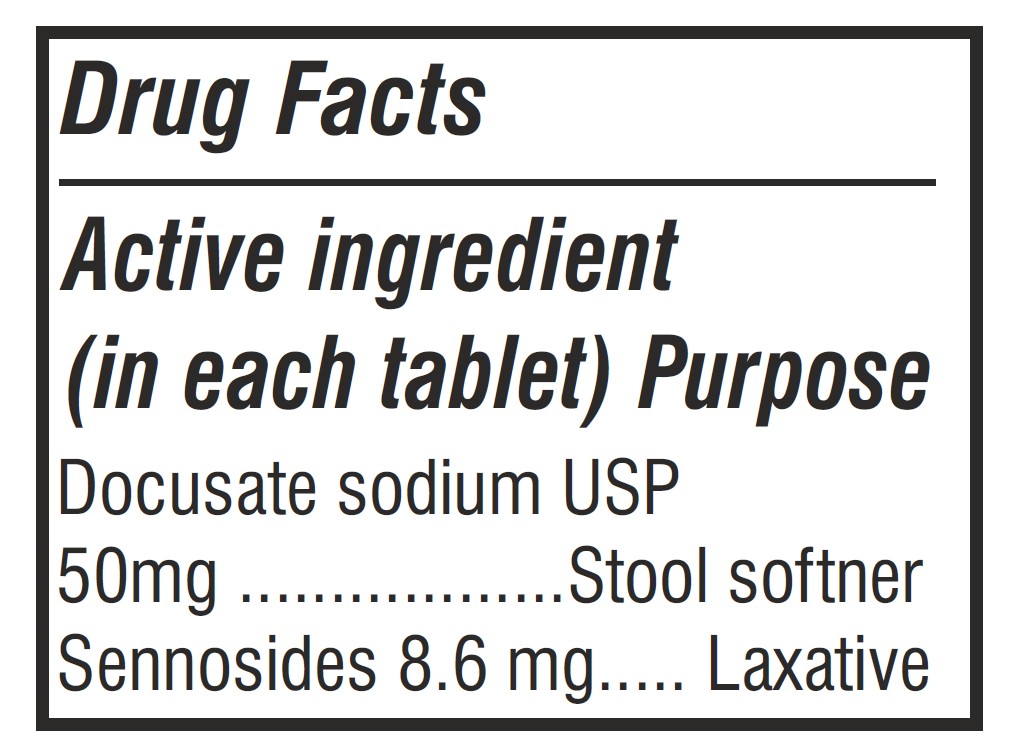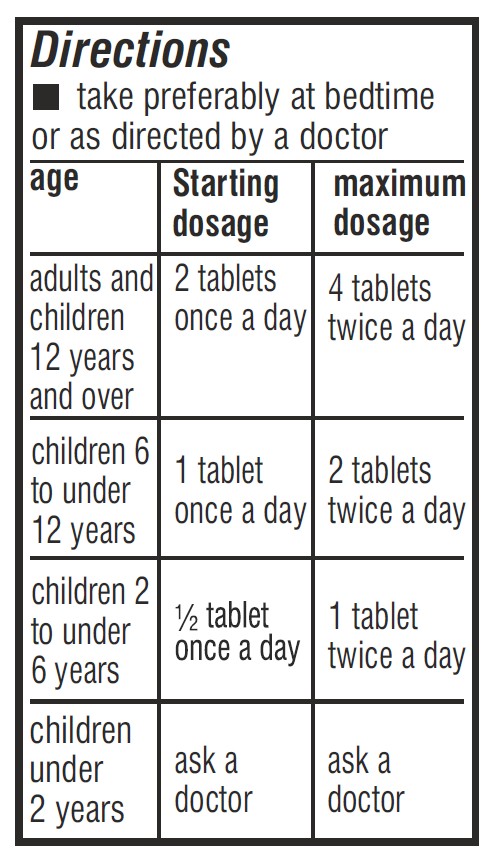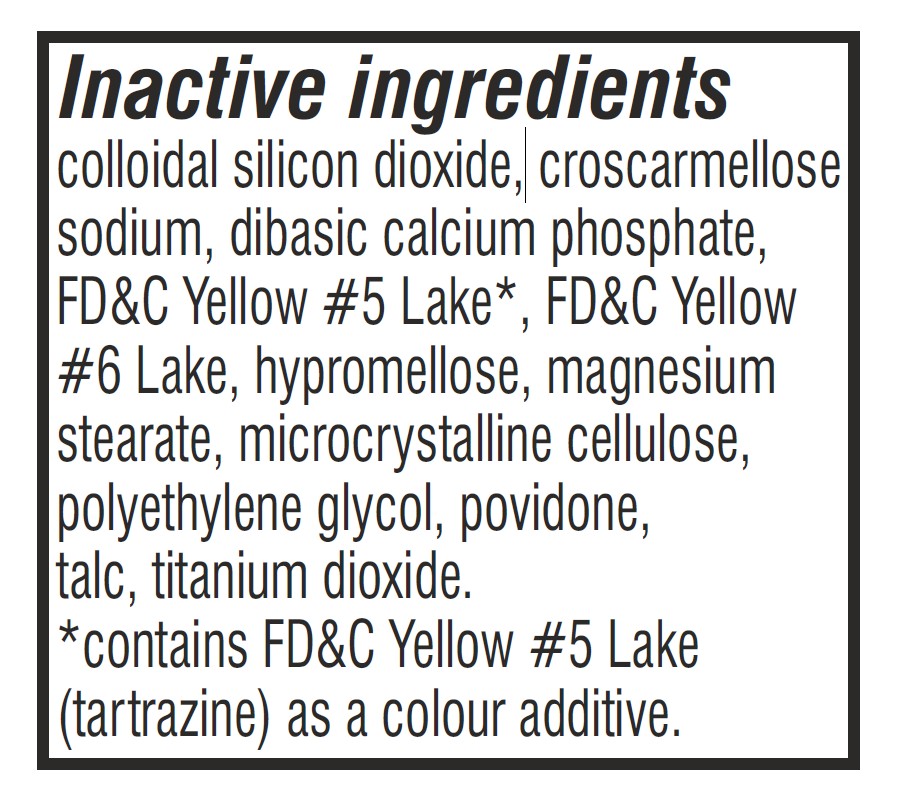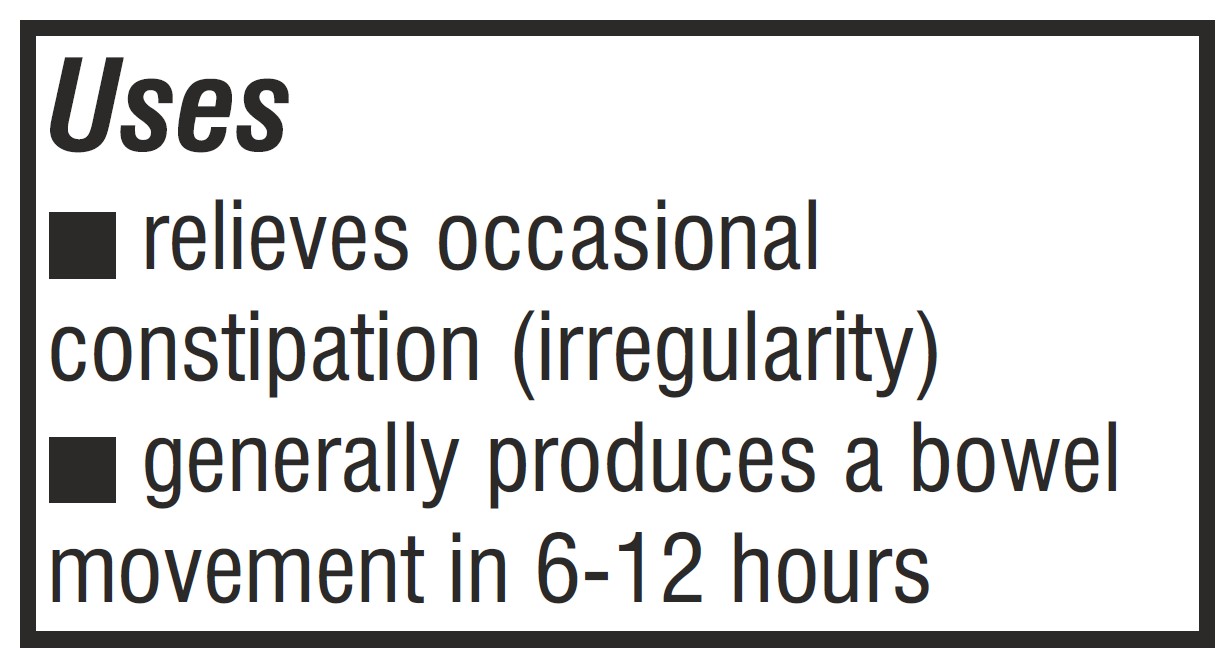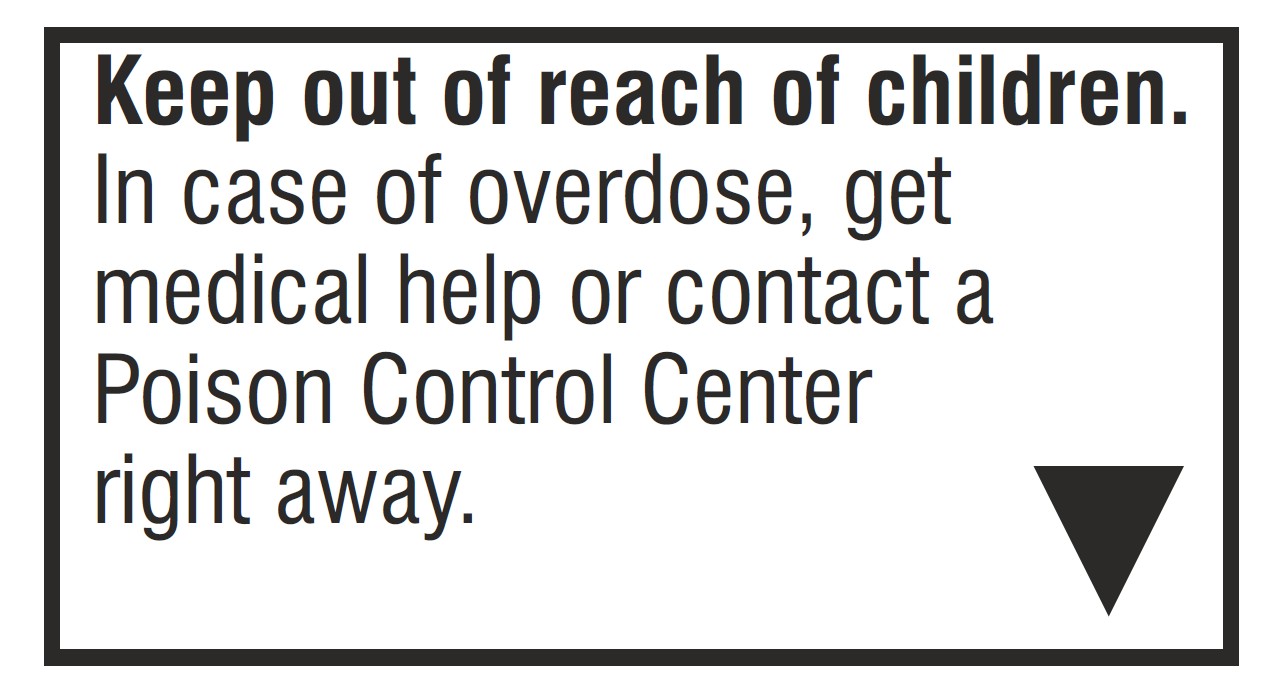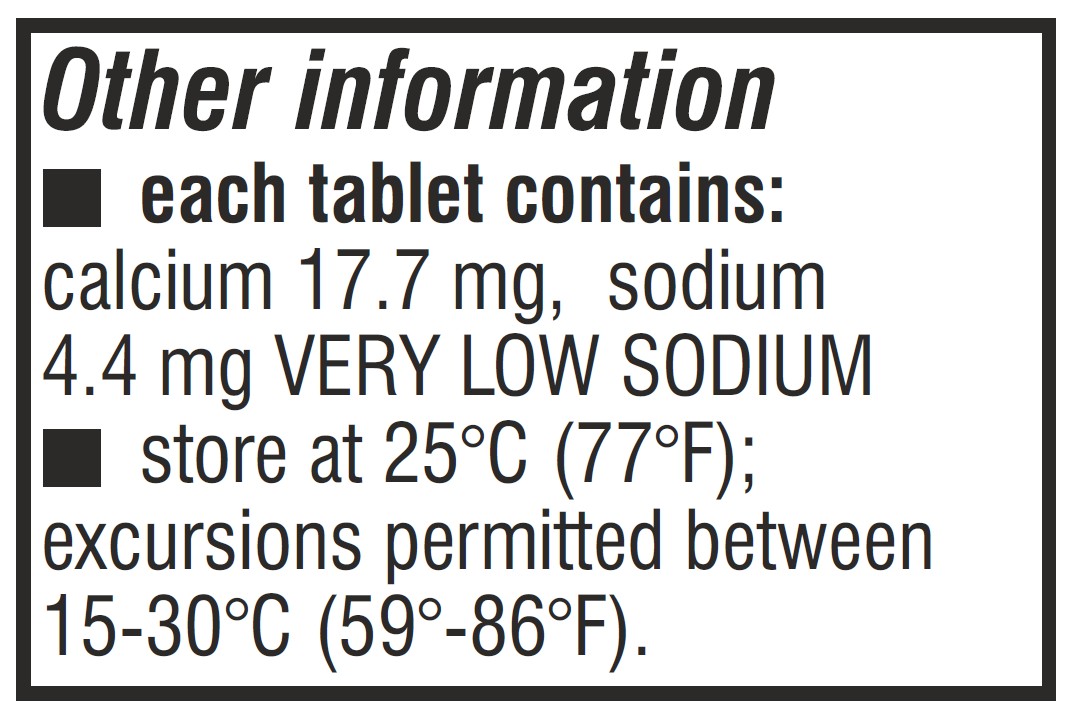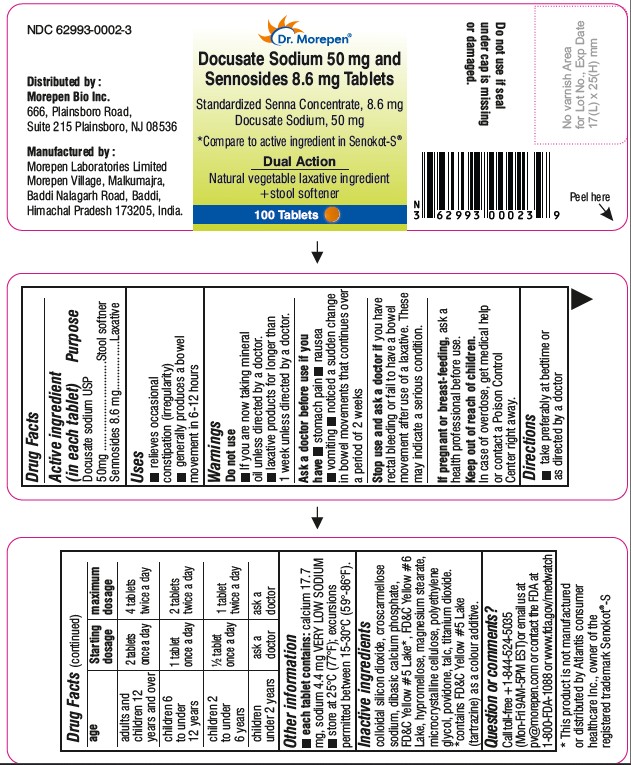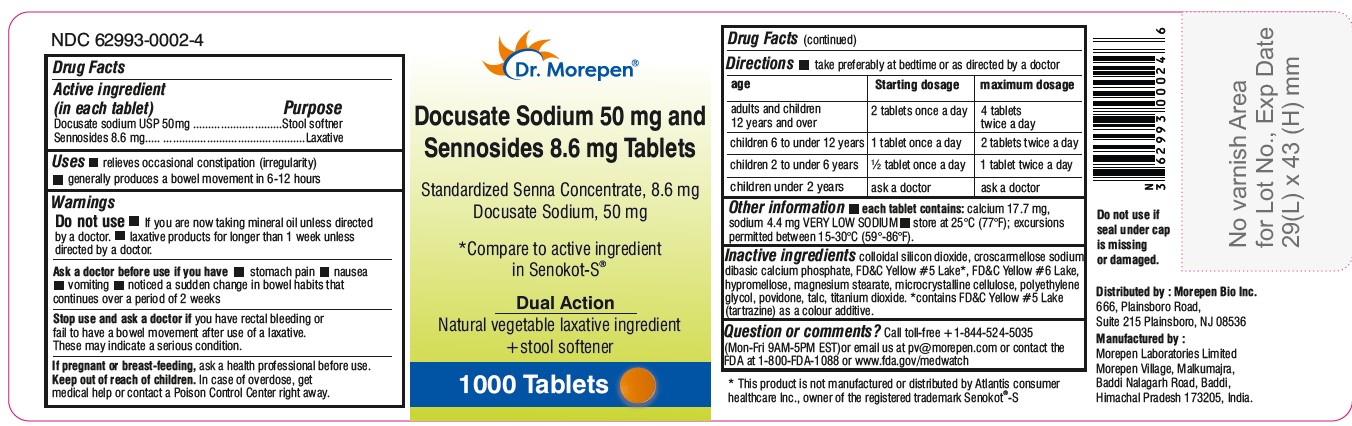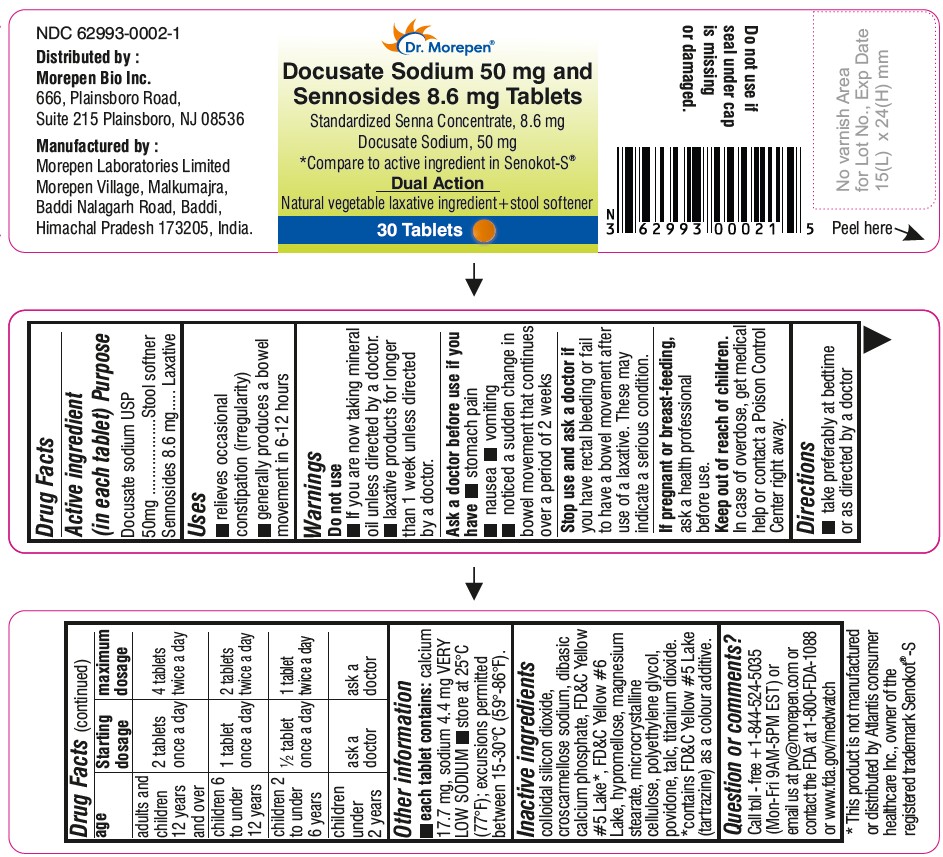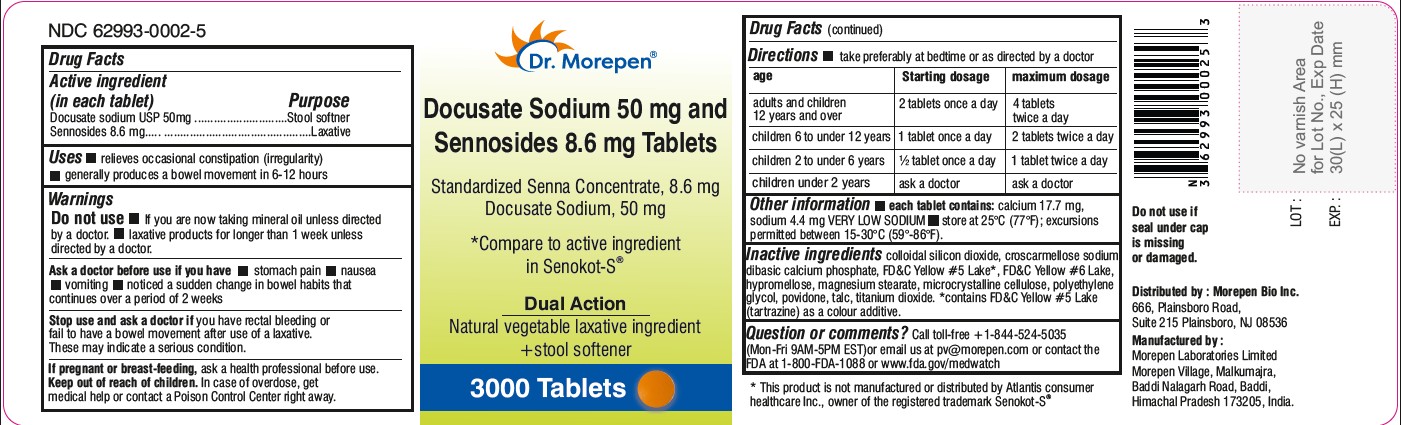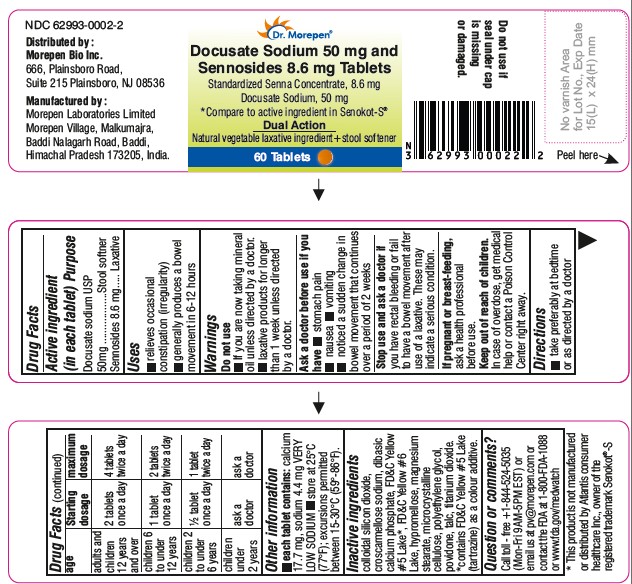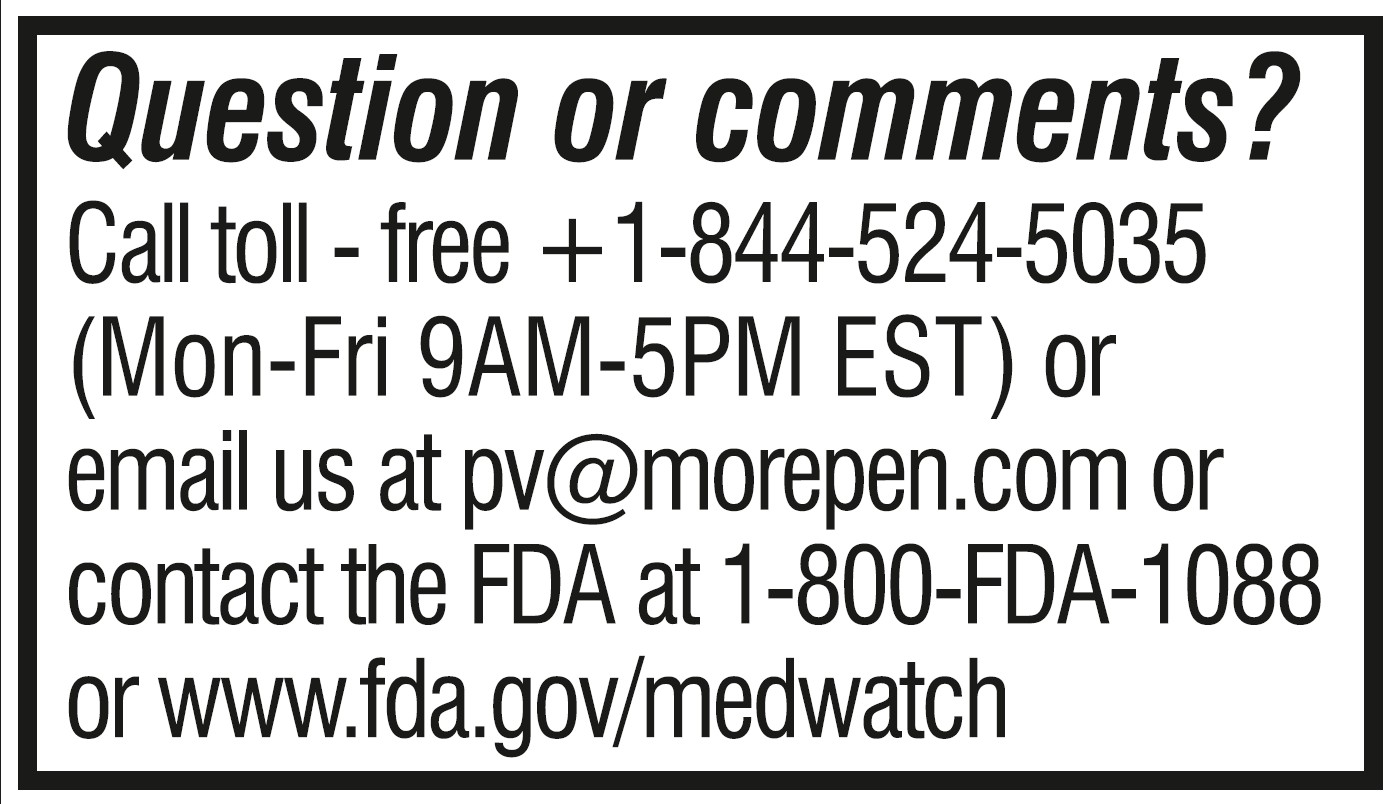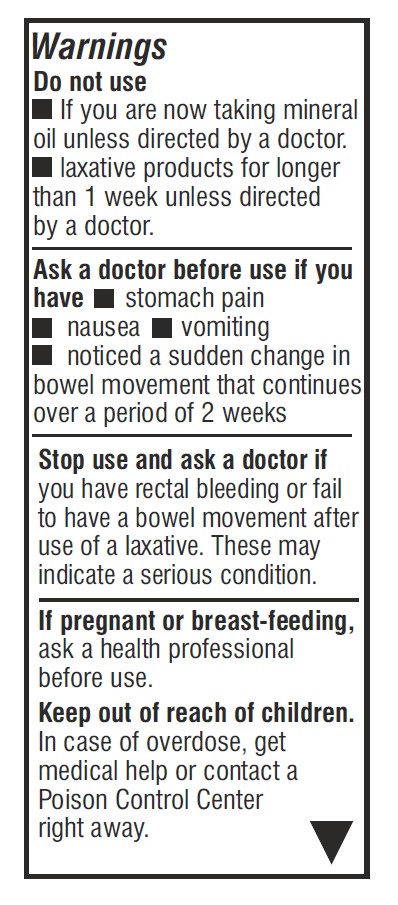 DRUG LABEL: Docusate Sodium and Sennosides
NDC: 62993-0002 | Form: TABLET
Manufacturer: Morepen Laboratories Limited
Category: otc | Type: HUMAN OTC DRUG LABEL
Date: 20260123

ACTIVE INGREDIENTS: DOCUSATE SODIUM 50 mg/1 1; SENNOSIDES 8.6 mg/1 1
INACTIVE INGREDIENTS: CALCIUM PHOSPHATE, DIBASIC, ANHYDROUS; TALC; POVIDONE K30; POLYETHYLENE GLYCOL, UNSPECIFIED; SILICON DIOXIDE; HYPROMELLOSE, UNSPECIFIED; TITANIUM DIOXIDE; CROSCARMELLOSE SODIUM; FD&C YELLOW NO. 6; MAGNESIUM STEARATE; MICROCRYSTALLINE CELLULOSE; FD&C YELLOW NO. 5

Docusate Sodium 50 mg and Sennosides 8.6 mg Tablets